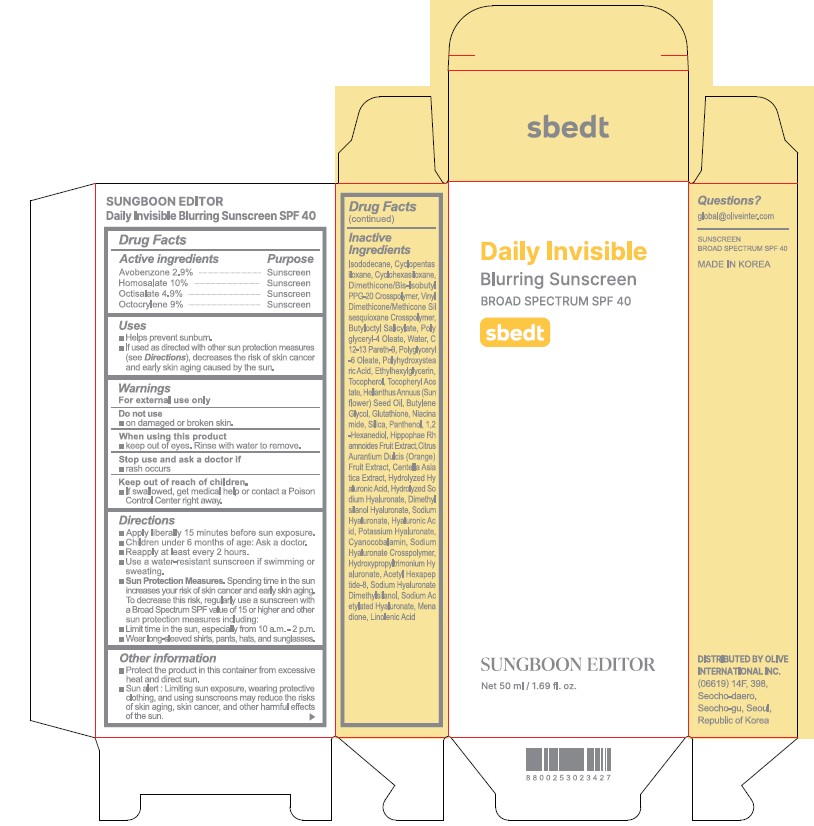 DRUG LABEL: Sungboon Editor Daily Invisible Blurring Sunscreen
NDC: 85037-002 | Form: CREAM
Manufacturer: Olive International Inc.
Category: otc | Type: HUMAN OTC DRUG LABEL
Date: 20250709

ACTIVE INGREDIENTS: AVOBENZONE 29 mg/1 mL; HOMOSALATE 100 mg/1 mL; OCTISALATE 49 mg/1 mL; OCTOCRYLENE 90 mg/1 mL
INACTIVE INGREDIENTS: 1,2-HEXANEDIOL; HIPPOPHAE RHAMNOIDES FRUIT; ORANGE; CENTELLA ASIATICA TRITERPENOIDS; DIMETHYLSILANOL HYALURONATE; HYALURONATE SODIUM; HYALURONIC ACID; CYANOCOBALAMIN; ACETYL HEXAPEPTIDE-8 AMIDE; SODIUM ACETYLATED HYALURONATE; MENADIONE; LINOLENIC ACID; SILICON DIOXIDE; ISODODECANE; CYCLOMETHICONE 5; CYCLOMETHICONE 6; DIMETHICONE/BIS-ISOBUTYL PPG-20 CROSSPOLYMER; VINYL DIMETHICONE/METHICONE SILSESQUIOXANE CROSSPOLYMER; BUTYLOCTYL SALICYLATE; POLYGLYCERYL-4 OLEATE; WATER; C12-13 PARETH-9; POLYGLYCERYL-6 OLEATE; POLYHYDROXYSTEARIC ACID (2300 MW); ETHYLHEXYLGLYCERIN; TOCOPHEROL; .ALPHA.-TOCOPHEROL ACETATE; SUNFLOWER OIL; BUTYLENE GLYCOL; GLUTATHIONE; NIACINAMIDE; PANTHENOL

85037-002_Sungboon Editor Daily Invisible Blurring Sunscreen

ACTIVE INGREDIENT

Homosalate 10%

Octocrylene 9.0%

Octisalate 4.9%

Avobenzone 2.9%

PURPOSE

Sunscreen

INDICATIONS AND USAGE

Helps prevent sunburn
If used as directed with other sun protection measures (see Directions) decrease the risk of skin cancer and early skin aging caused by the sun

DOSAGE AND ADMINISTRATION

Apply liberally 15 minutes before sun exposure

Children under 6 months or age: Ask a doctor.

Reapply at least every two hours
Use a water-resistant sunscreen if swimming or sweating
Sun protection measures. Spending time in the sun increases your risk of skin cancer and early skin aging. To decrease this risk, regularly use a sunscreen with a broad spectrum SPF or 15 of higher and other sun protection measures including:

Limited time in the sun, especially from 10 am to 2 pm.

Wear long-sleeve shirts, pants, hats, and sunglasses

WARNINGS

For external use only

Do not use on damaged or broken skin

When using this product, keep out of eyes. Rinse with water to remove.

Stop use and ask a doctor if rash occurs.

Keep out of reach of the children.

If swallowed, get medical help or contact a poison control center right away.

INACTIVE INGREDIENT

Isododecane, Cyclopentasiloxane, Cyclohexasiloxane, Dimethicone/Bis-Isobutyl PPG-20 Crosspolymer, Vinyl Dimethicone/Methicone Silsesquioxane Crosspolymer, Butyloctyl Salicylate, Polyglyceryl-4 Oleate, Water, C12-13 Pareth-9, Polyglyceryl-6 Oleate, Polyhydroxystearic Acid, Ethylhexylglycerin, Tocopherol, Tocopheryl Acetate, Helianthus Annuus (Sunflower) Seed Oil, Butylene Glycol, Glutathione, Niacinamide, Silica, Panthenol, 1,2-Hexanediol, Hippophae Rhamnoides Fruit Extract, Citrus Aurantium Dulcis (Orange) Fruit Extract, Centella Asiatica Extract, Hydrolyzed Hyaluronic Acid, Hydrolyzed Sodium Hyaluronate, Dimethylsilanol Hyaluronatem Sodium Hyaluronate, Hyaluronic Acid, Potassium Hyaluronate, Cyanocobalamin, Sodium Hyaluronate Crosspolymer, Hydroxypropyltrimonium Hyaluronate, Acetyl Hexapeptide-8, Sodium Hyaluronate Dimethylsilanol, Sodium Acetylated Hyaluronate, Menadione, Linolenic Acid

OTHER SAFETY INFORMATION

Protect the product in the container from excessive heat and direct sun.

Sun alaert: Limiting sun exposure, wearing protective clothing, and using suncreens may reduce the risks of skin aging, skin cancer, and other harmful effects of the sun.